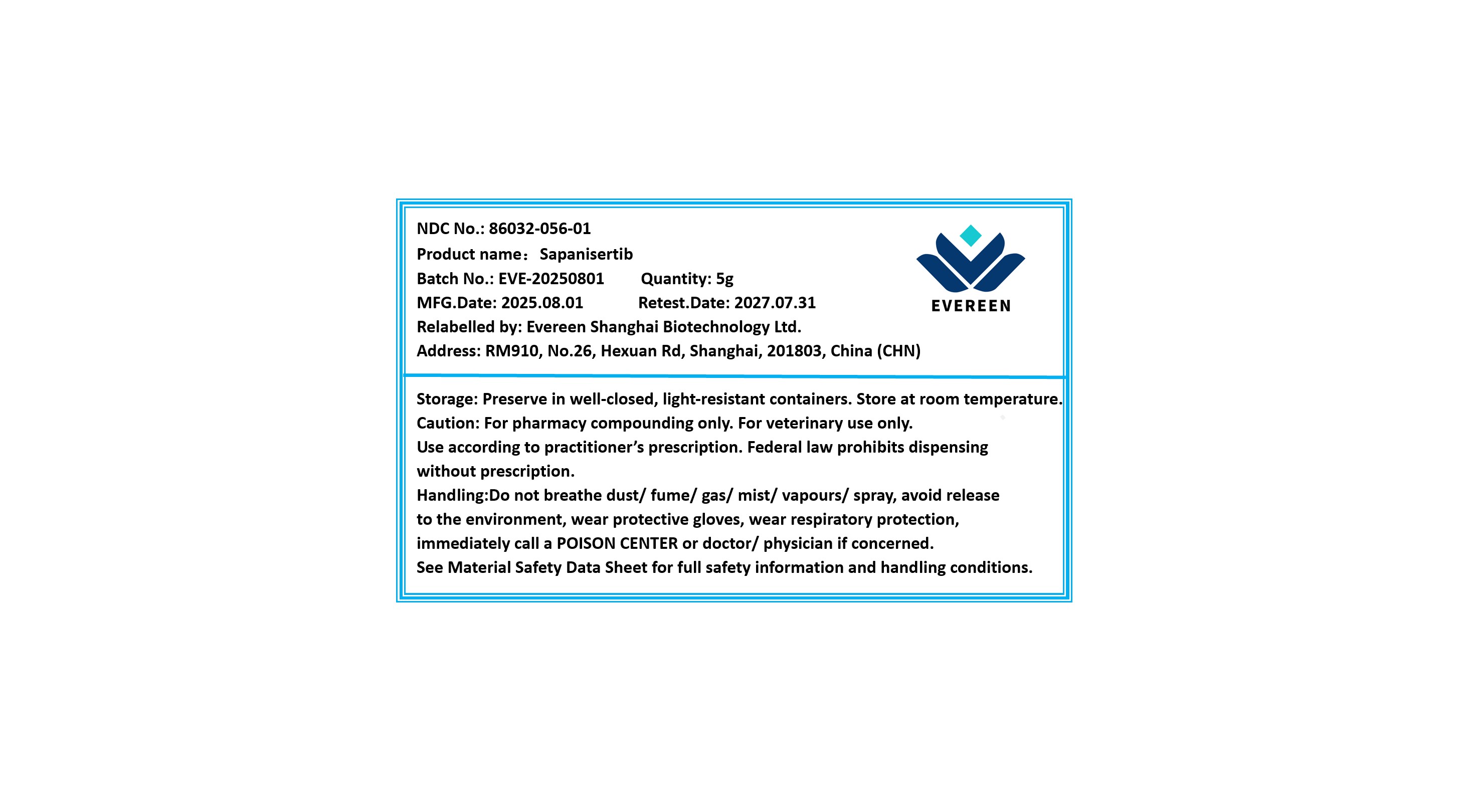 DRUG LABEL: Sapanisertib
NDC: 86032-056 | Form: POWDER
Manufacturer: Evereen Shanghai Biotechnology Ltd.
Category: other | Type: BULK INGREDIENT - ANIMAL DRUG
Date: 20250807

ACTIVE INGREDIENTS: SAPANISERTIB 1 g/1 g

Sapanisertib